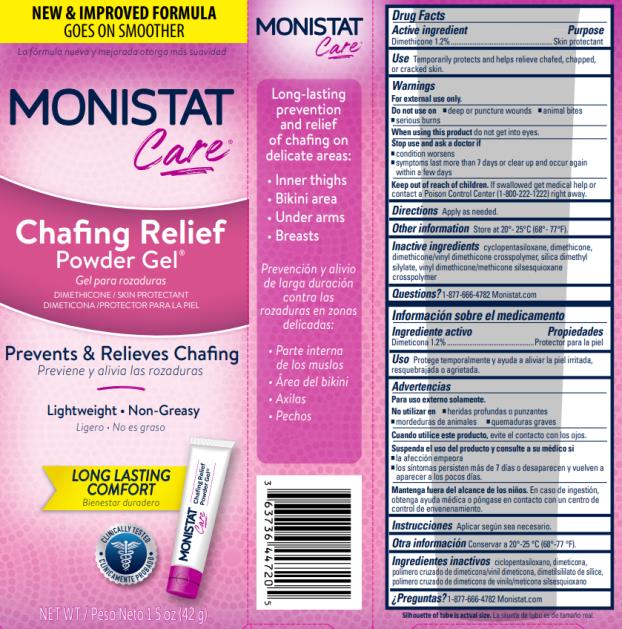 DRUG LABEL: Monistat Complete Care Chafing Relief
NDC: 63736-031 | Form: GEL
Manufacturer: Insight Pharmaceuticals LLC
Category: otc | Type: HUMAN OTC DRUG LABEL
Date: 20240419

ACTIVE INGREDIENTS: DIMETHICONE 1.2 g/100 g
INACTIVE INGREDIENTS: CYCLOMETHICONE 5; DIMETHICONE/VINYL DIMETHICONE CROSSPOLYMER (SOFT PARTICLE); SILICA DIMETHYL SILYLATE; VINYL DIMETHICONE/METHICONE SILSESQUIOXANE CROSSPOLYMER

Monistat Chafing Gel

Monistat Care Chafing Relief Powder Gel®

Drug Facts

Active ingredient

Dimethicone 1.2%

Purpose

Skin Protectant

Use

- Temporarily protects and helps relieve chafed, chapped or cracked skin.

Warnings

For external use only.

Do not use on

- deep or puncture wounds
- animal bites
- serious burns

When using this product

do not get into eyes.

Stop use and ask a doctor if

- condition worsens
- symptoms last more than 7 days or clear up and occur again within a few days

Keep out of reach of children.

If swallowed get medical help or contact a Poison Control Center (1-800-222-1222) right away.

Directions

Apply as needed.

Other information

Store at 20˚-25˚C (68˚-77˚F)

Inactive ingredients

cyclomethicone, dimethicone, dimethicone/vinyl dimethicone crosspolymer, silica dimethyl silylate, vinyl dimethicone/methicone silsesquioxane crosspolymer

Questions?

1-877-666-4782 Monistat.com

PRINCIPAL DISPLAY PANEL

MONISTAT
Care®
Chafing Relief Powder Gel®
DIMETHICONE /SKIN PROTECTANT
NET WT/ Peso Neto 1.5 oz (42g)